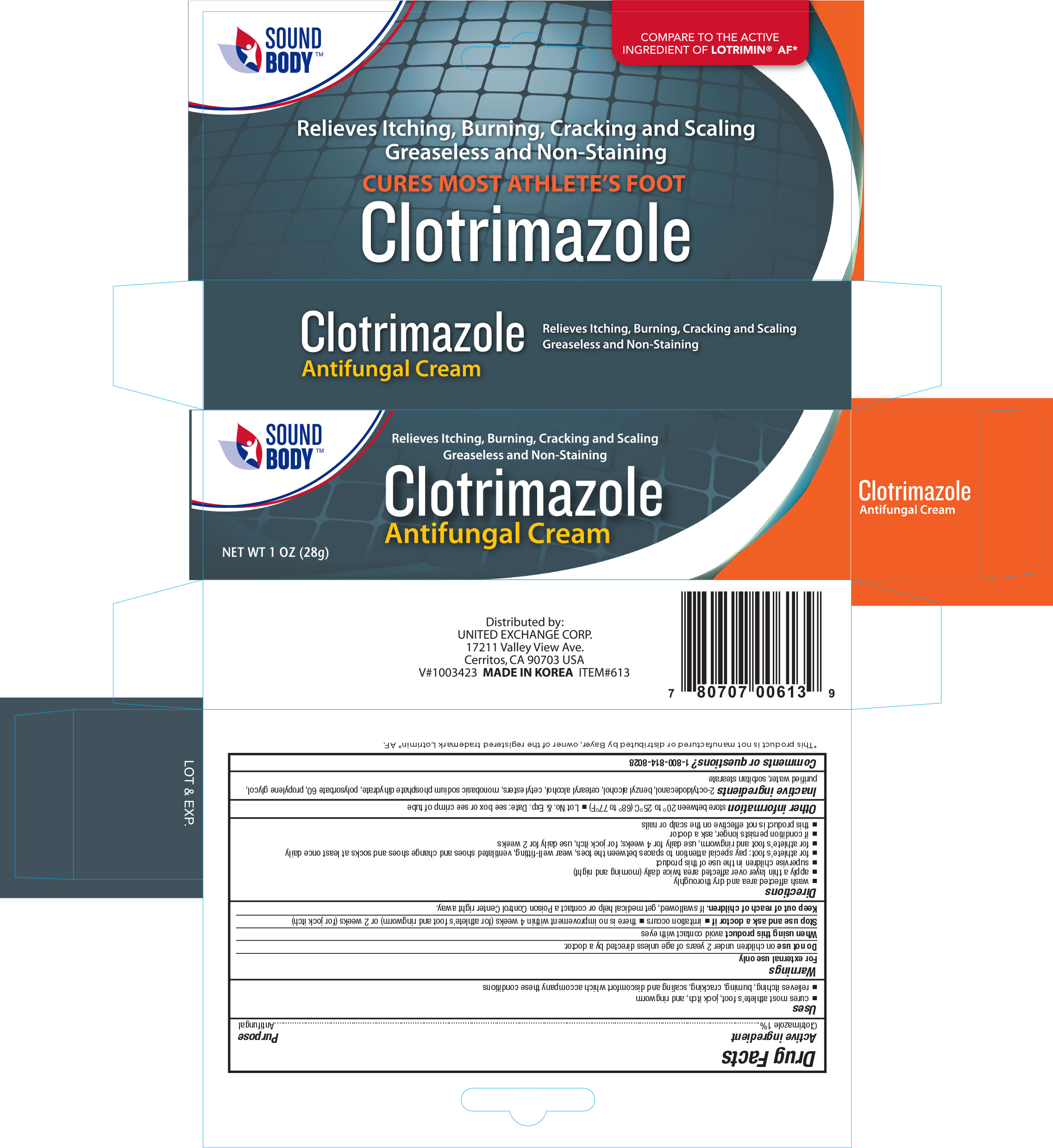 DRUG LABEL: SoundBody Clotrimazole Antifungal
NDC: 65923-139 | Form: CREAM
Manufacturer: United Exchange Corp.
Category: otc | Type: HUMAN OTC DRUG LABEL
Date: 20170705

ACTIVE INGREDIENTS: CLOTRIMAZOLE 10 mg/1 g
INACTIVE INGREDIENTS: OCTYLDODECANOL; BENZYL ALCOHOL; CETOSTEARYL ALCOHOL; CETYL ESTERS WAX; MAGNESIUM PHOSPHATE, MONOBASIC, DIHYDRATE; POLYSORBATE 60; PROPYLENE GLYCOL; WATER; SORBITAN MONOSTEARATE

Active ingredients Purpose

Clotrimazole 1%.......................... Antifungal

Uses

- Cures most athletes foot, jock itch, and ringworm
- relieves itching, burning, cracking, scaling and discomfort which accompany these conditions

Warnings

For external use only

Do not use on children under 2 years of age unless directed by a doctor.

Stop use and ask a doctor if

- irritation occurs
- there is no improvement within 4 weeks (for athlete's foot and ringworm) or 2 weeks (for jock itch)

Keep out of reach of children. If swallowed, get medical help or contact a Poison Control Center right away.

Directions

- wash affected area and dry thoroughly
- apply a thin layer over affected area twice daily (morning and night)
- supervise children in the use of this product
- for athlete's foot: pay special attention to spaces between the toes, wear well-fitting, ventilated shoes, and change shoes and socks at least once a day
- for athlete's foot and ringwom use daily for 4 weeks; for jock itch; use daily for 2 weeks
- this product is not effective on the scalp or nails

Other information

- store between 20° to 25°C (68° to 77°F)
- Lot No. & Exp. Date: see box or see crimp of tube

Inactive ingredients

2-octyldodecanol, benzyl alcohol, cetostearyl alcohol, cetyl esters, monobasic sodium phosphate dihydrate, polysorbate 60, propylene glycol, purified water, sorbitan stearate

DOSAGE AND ADMINISTRATION

DISTRIBUTED BY:

UNITED EXCHANGE CORP.

17211 VALLEY VIEW AVE.

CERRITOS, CA 90703 USA